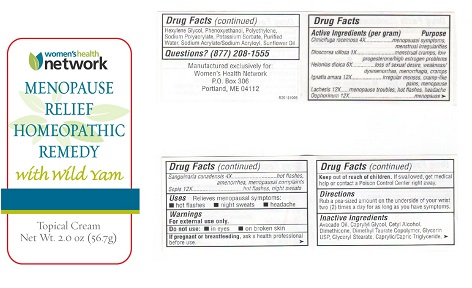 DRUG LABEL: Menopause Relief Homeopathic Remedy
NDC: 61727-054 | Form: CREAM
Manufacturer: Homeocare Laboratories Inc.
Category: homeopathic | Type: HUMAN OTC DRUG LABEL
Date: 20151230

ACTIVE INGREDIENTS: SANGUINARIA CANADENSIS ROOT 4 [hp_X]/60 mL; STRYCHNOS IGNATII SEED 12 [hp_X]/60 mL; LACHESIS MUTA WHOLE 12 [hp_X]/60 mL; DIOSCOREA VILLOSA ROOT 1 [hp_X]/60 mL; ACTAEA CIMICIFUGA ROOT 4 [hp_X]/60 mL; CHAMAELIRIUM LUTEUM ROOT 6 [hp_X]/60 mL; SEPIA ESCULENTA WHOLE 12 [hp_X]/60 mL; SUS SCROFA OVARY 12 [hp_X]/60 mL
INACTIVE INGREDIENTS: GLYCERIN; 2,4-DIAMINO-5-METHYLPHENOXYETHANOL HYDROCHLORIDE; POTASSIUM SORBATE; POLYETHYLENE OXIDE 1000000; WATER; SODIUM ACRYLATE/SODIUM ACRYLOYLDIMETHYLTAURATE COPOLYMER (4000000 MW); CAPRYLIC/CAPRIC/LAURIC TRIGLYCERIDE; AVOCADO OIL; CAPRYLYL GLYCOL; DIMETHICONE 1000; HYDROXYETHYL ACRYLATE/SODIUM ACRYLOYLDIMETHYL TAURATE COPOLYMER (45000 MPA.S AT 1%); GLYCERYL STEARATE SE; HEXYLENE GLYCOL; SODIUM POLYACRYLATE (8000 MW); SUNFLOWER OIL; CETYL ALCOHOL

PURPOSE

Relieves Menopausal Symptoms

ACTIVE INGREDIENTS

Dioscorea villosa
Cimicifuga racemosa
Sanguinaria Canadensis
Ignatia amara
Helonias dioica
Sepia
Oophorinum
Lachesis

INACTIVE INGREDIENTS

Avocado Oil
Caprylyl Glycol
Cetyl Alcohol
Dimethicone
Dimethyl Taurate Copolymer
Glycerin USP
Glyceryl Stearate
Hexylene Glycol
Phenoxyethanol
Polyethylene
Sodium Polyacrylate
Potassium Sorbate
Purified Water
Sodium Acrylate/Sodium Acryloyl
Sunflower Oil
Caprylic/Capric Triglyceride

KEEP OUT OF REACH OF CHILDREN

If swallowed, get meical help or contact a poison control center right away.

QUESTIONS?

(877) 208-1555

DIRECTIONS

Rub a pea-sied amount on the underside of your wrist two (2) times a day for as long as you have symptoms.

DO NOT USE

In eyes, or on broken skin

If pregnant or breastfeeding, ask a health professional before use.

WARNINGS

For external use only

USES

Relieves menopausal symptoms

Hot flashes, night sweats, headaches